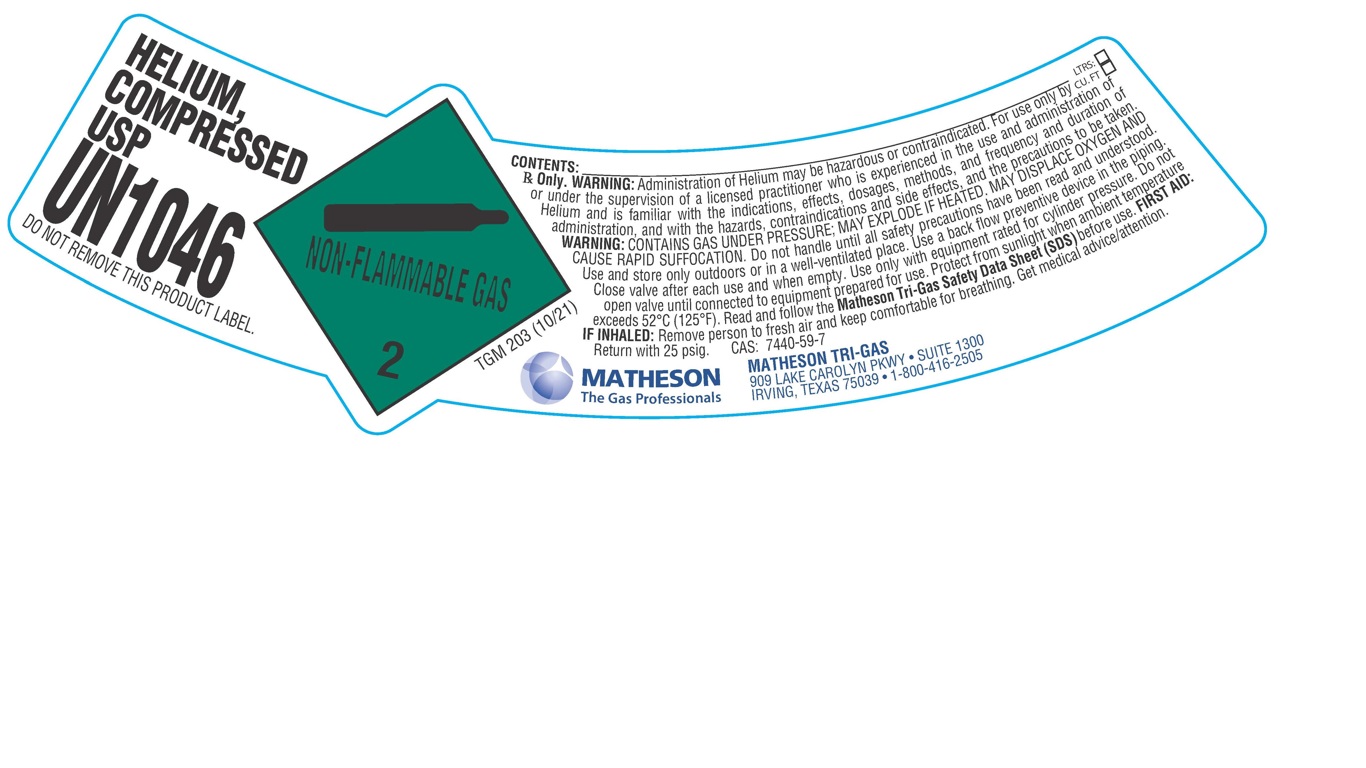 DRUG LABEL: Helium
NDC: 55037-512 | Form: GAS
Manufacturer: Matheson Tri-Gas, Inc.
Category: animal | Type: PRESCRIPTION ANIMAL DRUG LABEL
Date: 20251202

ACTIVE INGREDIENTS: Helium 992 mL/1 L

Helium

PACKAGE LABEL

HELIUM, COMPRESSED USP

UN1046

DO NOT REMOVE THIS PRODUCT LABEL.

CONTENTS: LTRS: CU.FT:

Rx Only. WARNING: Administration of Helium may be hazardous or contraindicated. For use only by or under the supervision of a licensed practitioner who is experienced in the use and administration of Helium and is familiar with the indications, effects, dosages, methods, and frequency and duration of administration, and with the hazards, contraindications and side effects, and the precautions to be taken. WARNING: CONTAINS GAS UNDER PRESSURE; MAY EXPLODE IF HEATED. MAY DISPLACE OXYGEN AND CAUSE RAPID SUFFOCATION. Do not handle until all safety precautions have been read and understood. Use and store only outdoors or in a well-ventilated place. Use a back flow preventive device in the piping. Close valve after each use and when empty. Use only with equipment rated for cylinder pressure. Do not open valve until connected to equipment prepared for use. Protect from sunlight when ambient temperature exceeds 52 C (125 F). Read and follow the Matheson Tri-Gas Safety Data Sheet (SDS) before use. FIRST AID: IF INHALED: Remove person to fresh air and keep comfortable for breathing. Get medical advice/attention. Return with 25 psig. CAS: 7440-59-7

MATHESON The Gas Professionals

MATHESON TRI-GAS

909 LAKE CAROLYN PKWY. SUITE 1300

IRVING, TEXAS 75039 . 1-800-416-2505